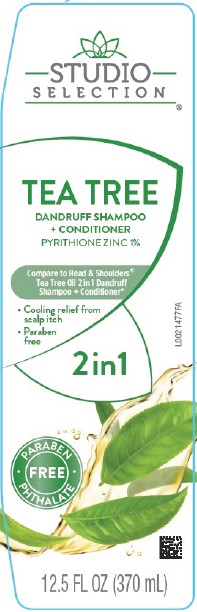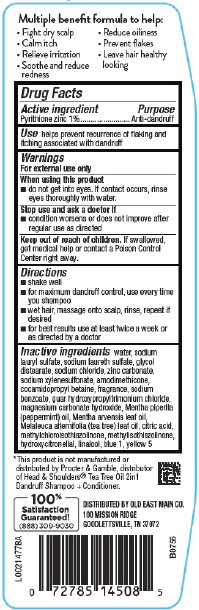 DRUG LABEL: Pyrithione zinc
NDC: 75712-470 | Form: SHAMPOO
Manufacturer: Old East Main Co.
Category: otc | Type: HUMAN OTC DRUG LABEL
Date: 20260302

ACTIVE INGREDIENTS: PYRITHIONE ZINC 10 mg/1 mL
INACTIVE INGREDIENTS: WATER; SODIUM LAURYL SULFATE; SODIUM LAURETH SULFATE; GLYCOL DISTEARATE; SODIUM CHLORIDE; ZINC CARBONATE; SODIUM XYLENESULFONATE; AMODIMETHICONE (800 CST); COCAMIDOPROPYL BETAINE; SODIUM BENZOATE; GUAR HYDROXYPROPYLTRIMONIUM CHLORIDE (1.7 SUBSTITUENTS PER SACCHARIDE); MAGNESIUM CARBONATE HYDROXIDE; PEPPERMINT OIL; MENTHA ARVENSIS LEAF OIL; TEA TREE OIL; CITRIC ACID MONOHYDRATE; METHYLCHLOROISOTHIAZOLINONE; METHYLISOTHIAZOLINONE; HYDROXYCITRONELLAL; LINALOOL, (+/-)-; FD&C BLUE NO. 1; FD&C YELLOW NO. 5

Studio Selection 470.000/470AB
Tea Tree 2 in 1 Dandruff Shampoo and Conditioner

claims

Multiple Benefit formula to help:

- Fight dry scalp
- Calm itch
- Relieve irritation
- Soothe and reduce redness
- Reduce oiliness
- Prevent flakes
- Leave hair healthy looking

Active ingredient

Pyrithione Zinc 1%

Purpose

Anti-dandruff

Use

helps prevent recurrence of flaking and itching associated with dandruff

Warnings

For external use only

When using this product

- do not get into eyes. If contact occurs, rinse eyes thoroughly with water.

Stop use and ask a doctor if

- condition worsens or does not improve after regular use as directed

Keep out of reach of children.

If swallowed, get medical help or contact a Poison Control Center right away.

Directions

- shake well
- for maximum dandruff controll, use every time you shampoo
- wet hair, massage onto scalp, rinse, repeat if desired
- for best results use at least twice a week or as directed by a doctor

inactive ingredients

water, sodium lauryl sulfate, sodium laureth sulfate, glycol distearate, sodium chloride, zinc carbonate, sodium xylenesulfonate, amodimethicone, cocamidopropyl betaine, fragrance, sodium benzoate, guar hydroxypropyltrimonium chloride, magnesium carbonate hydroxide, Mentha piperita (peppermint) oil, Mentha arvensis leaf oil, Melaleuca alternifolia (tea tree) leaf oil, citric acid, methylchloroisothiazolinone, methylisothiazolinone, hydroxycitronellal, linalool, blue 1, yellow 5

Disclaimer

*This product is not manufactured or distributed by Procter & Gamble, the distributor of Head & Shoulders® Tea Tree Oil 2in1 Dandruff Shampoo + Conditioner.

Adverse Reactions

100% Satisfaction Guaranteed!

(888)309-9030

DISTRIBUTED BY OLD EAST MAIN CO.

100 MISSION RIDGE

GOODLETTSVILLE, TN 37072

Principal display panel

STUDIO

SELECTION®

TEA TREE

DANDRUFF SHAMPOO + CONDITIONER

PYRITHIONE ZINC 1%

Compare to Head & Shoulders® Tea Tree Oil 2 in 1 Dandruff Shampoo & Conditioner*

- Cooling relief from scalp itch
- Paraben free

2in1

Paraben + Phthalate Free

12.5 FL OZ (370 mL)